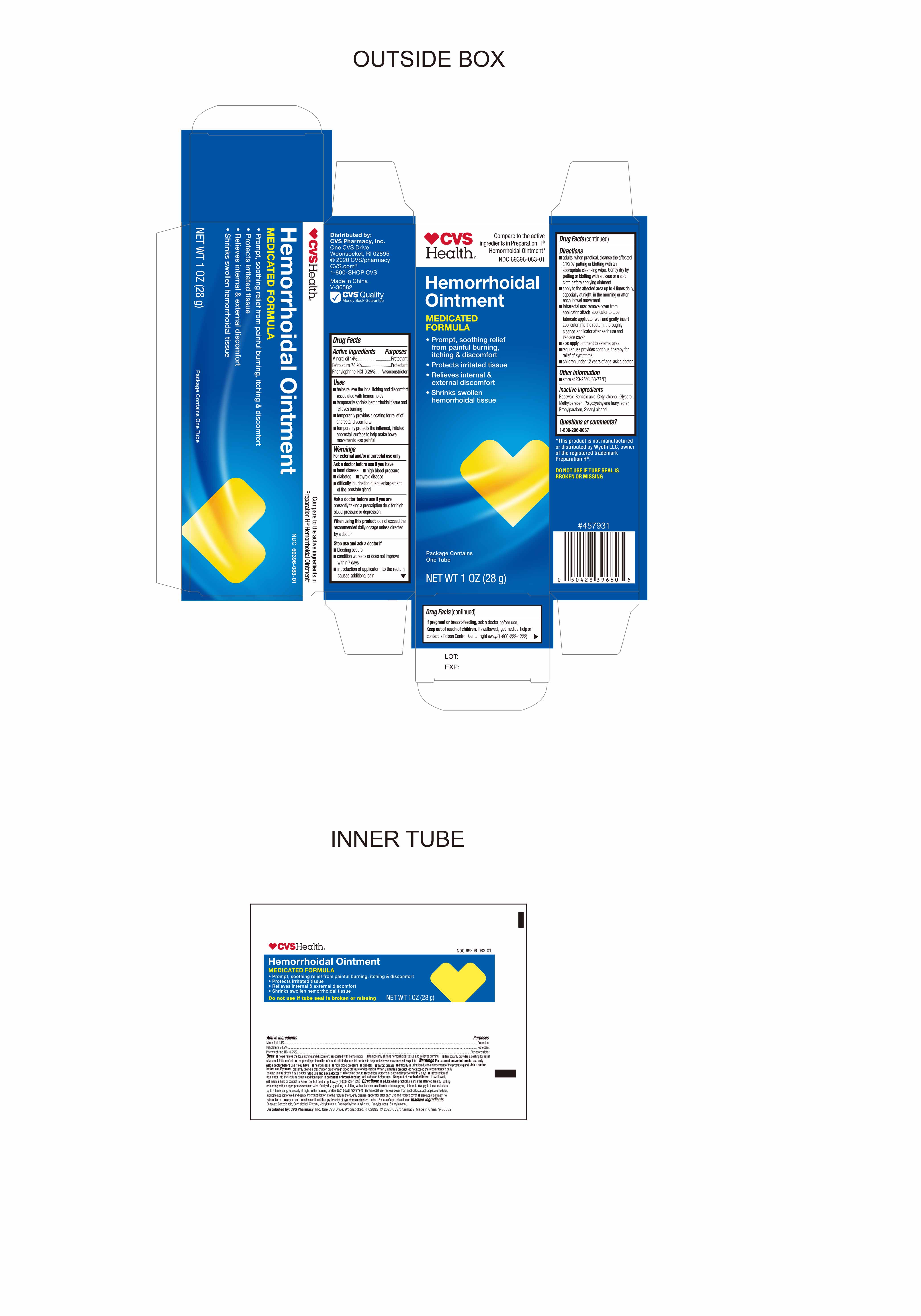 DRUG LABEL: HemorrhoidalOintment
NDC: 69396-083 | Form: OINTMENT
Manufacturer: Trifecta Pharmaceuticals USA LLC
Category: otc | Type: HUMAN OTC DRUG LABEL
Date: 20241218

ACTIVE INGREDIENTS: PETROLATUM 74.9 g/100 g; PHENYLEPHRINE HYDROCHLORIDE 0.25 g/100 g; MINERAL OIL 14 g/100 g
INACTIVE INGREDIENTS: CETYL ALCOHOL; LAURETH-23; BENZOIC ACID; PROPYLPARABEN; METHYLPARABEN; YELLOW WAX; GLYCERIN; STEARYL ALCOHOL

CVS Hemorrhoidal Ointment

Active Ingredient

Phenylephrine HCI 0.25%

Purpose

Vasoconstrictor

Active Ingredient

Mineral Oil 14%

Purpose

Protectant

Active Ingredient

Petrolatum 74.9%

Purpose

Protectant

Uses

- Helps relieve the local itching and discomfort associated with hemorrhoids
- Temporarily shrinks hemorrhoidal tissue and relieves burning
- Temporarily provides a coating for relief of anorectal discomforts
- Temporarily profects the inflamed, irritated anorectal surface to help make bowel movements less painful

Warnings

For external and/or anorectal use only

Ask doctor before use if you have

- heart disease
- high blood pressure
- thyroid disease
- diabetes
- difficulty in urination due to enlargement of the prostate gland

Ask doctor before use if you are presently taking a prescription drug for high blood pressure or depression

Stop Use and Ask Doctor if

- Bleeding occurs
- Condition worsens or does not improve within 7 days
- Introduction of applicator into the rectum causes additional pain

If Pregnant or Breast-Feeding

Ask a doctor before use

Keep out of reach of children

If swallowed get medical help or contact a Poison Control Center right away (1-800-222-1222).

Directions

Adults:

- When practical, cleanse the affected area by patting or blotting with an appropriate cleansing wipe. Gently dry by patting or blotting with a tissue or a soft cloth before applying ointment.
- Apply to the affected area up to 4 times daily, especially at night, in the morning or after each bowel movement.
- Intrarectal Use: remove cover from applicator, attach applicator to tube, lubricate applicator well and gently insert applicator into the rectum, thoroughly cleanse applicator after each use and replace cover.
- Also apply ointment to external area
- Regular use provides continual therapy for relief of symptoms
- Children under 12 years of age: ask a doctor

Other Information

- Store at room temperature 20°-25°C (68°-77°F)
- Do not use if tube seal is broken or missing

Questions? Call 1-888-296-9067

Inactive Ingredients

Beeswax, Benzoic Acid, Cetyl alcohol, Glycerol Methylparaben, Polyoxyethylene lauryl ether, Propylparaben, Stearyl alcohol

Other Information

Distributed By:

CVS Pharmacy Inc.

One CVS Drive

Woodsocket, RI 02895

CVS.com

1 800 SHOP CVS

Made in China

V36582